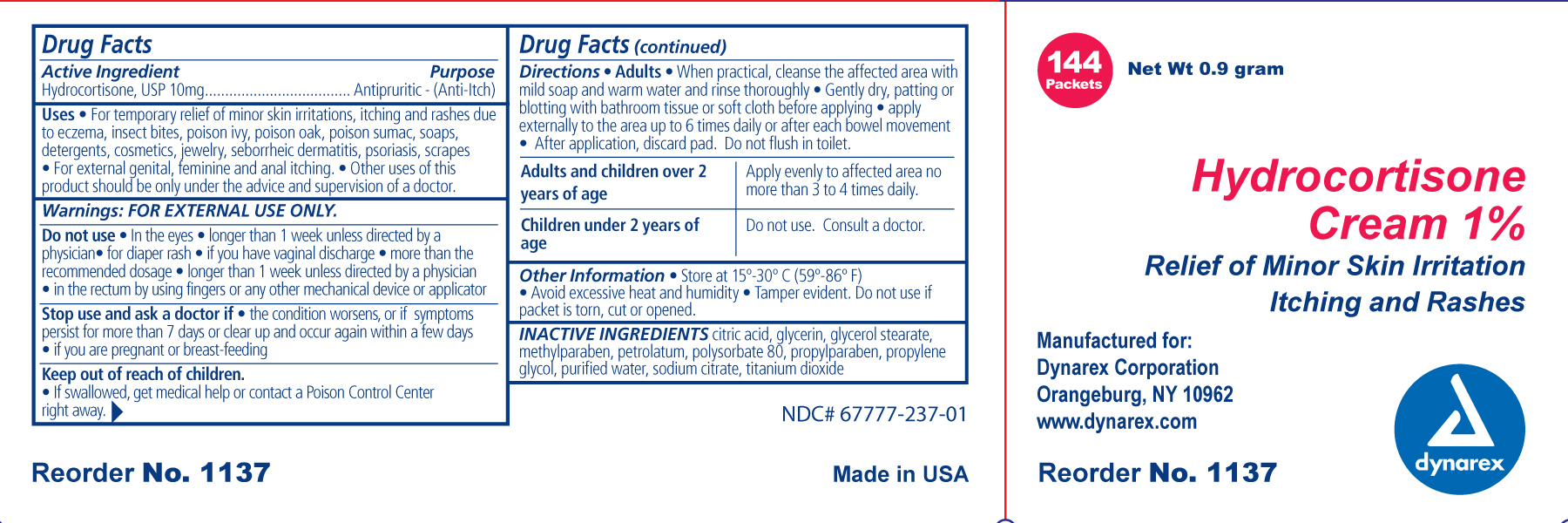 DRUG LABEL: Hydrocortisone
NDC: 67777-237 | Form: CREAM
Manufacturer: Dynarex Corporation
Category: otc | Type: HUMAN OTC DRUG LABEL
Date: 20110315

ACTIVE INGREDIENTS: HYDROCORTISONE 1 g/100 g
INACTIVE INGREDIENTS: CITRIC ACID MONOHYDRATE; GLYCERIN; GLYCERYL MONOSTEARATE; METHYLPARABEN; PETROLATUM; POLYSORBATE 80; PROPYLENE GLYCOL; SODIUM CITRATE; TITANIUM DIOXIDE; WATER; PROPYLPARABEN

Hydrocortisone

Active Ingredient Purpose

Hydrocortisone USP 10 mg Antipruritic (anti-itch)

Uses:

For temporary relief of;

- minor skin irritations, inflammation and rashes due to

- eczema
- insect bites
- poison ivy
- poison oak
- poison sumac
- soaps
- detergents
- cosmetics
- jewelry
- seborrheic dermatitis
- psoriasis
- scrapes

and for external itching of;

- genital
- feminine and
- anal itching

- other uses of this product should be only under the advice and supervision of a doctor

Warnings:

For external use only

Do not use:

- in the eyes
- longer than 1 week unless directed by a physician
- for diaper rash
- if you have vaginal discharge
- more than the recommended daily dosage unless directed by a doctor
- in the rectum bu using fingers or any other mechanical device or applicator

Stop use and ask a physician if:

- the condition persists or gets worse
- symptoms clear up and occur again within a few days
- you are pregnant or breast feeding

Keep out of reach of children

- If swallowed, get medical help or contact a Poison Control Center right away.

Directions:

Adults and children over 2 years of age

- Apply evenly to affected area no more than 3 or 4 times daily.

Children under 2 years of age

- Do not use
- consult a physician

Adults

- When practical, cleanse the affected area with mild soap and warm water and rinse thoroughly
- Gently dry, patting and blotting with bathroom tissue or soft cloth before applying
- apply externally to the area up to 6 times daily or after each bowel movement

Other information:

- Store at a controlled room temperature 15 deg - 30 deg C (59 deg - 86 deg F)
- Avoid excessive heat and humidity
- tamper evident, do not use if packet is torn, cut or open

Inactive ingredients:

citric acid, glycerin, glycerol stearate, methylparaben, petrolatum, polysorbate 80, propyl paraben, propylene glycol, purified water, sodium citrate, titanium dioxide,

Indications and Usage

For temporary relief of minor skin irritations and external itching.

PACKAGE LABEL

Principal Display